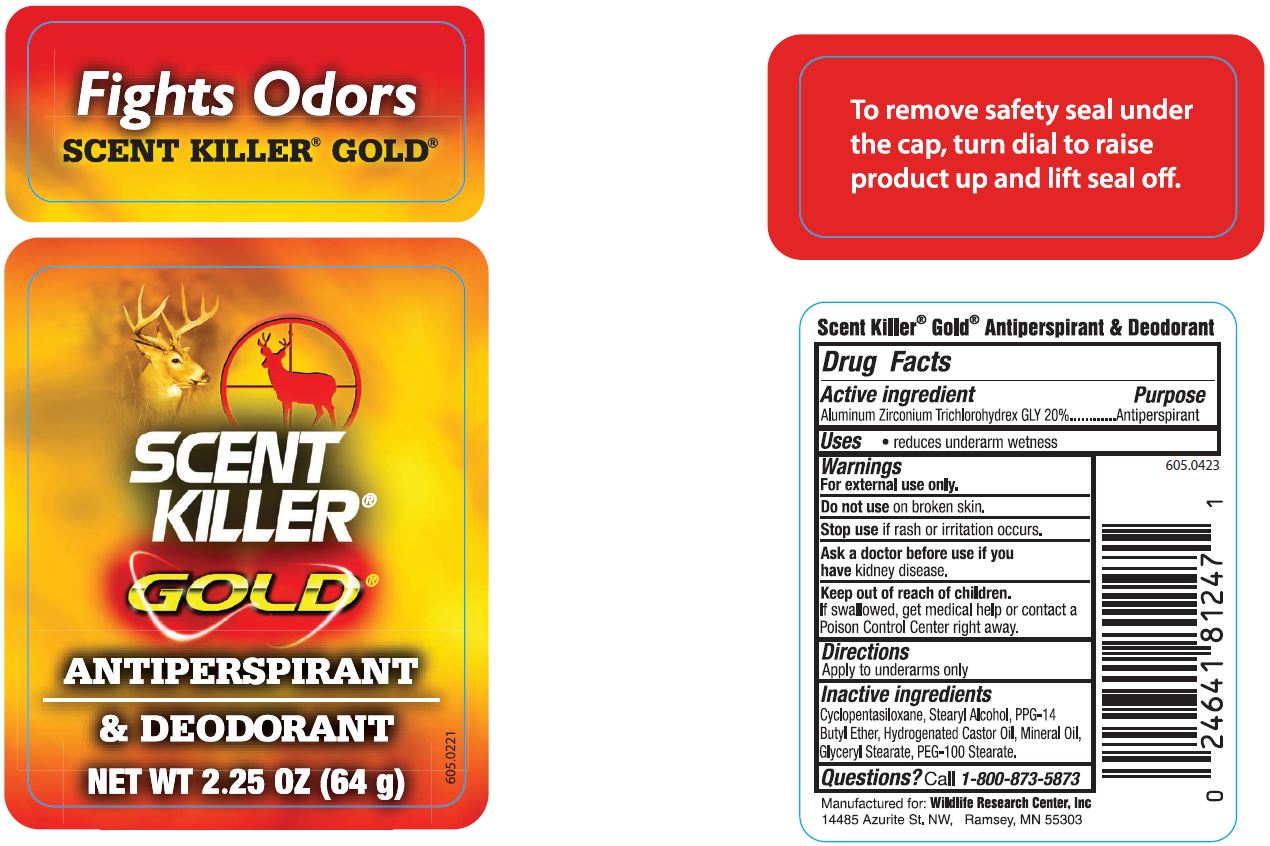 DRUG LABEL: Scent Killer
NDC: 64776-416 | Form: STICK
Manufacturer: Wildlife Research Center, Inc
Category: otc | Type: HUMAN OTC DRUG LABEL
Date: 20240710

ACTIVE INGREDIENTS: ALUMINUM ZIRCONIUM TETRACHLOROHYDREX GLY 12.8 g/64 g
INACTIVE INGREDIENTS: STEARYL ALCOHOL 12.16 g/64 g

Wildlife Research Center, inc (Scent Killer Gold AP)

Drug Facts

Active ingredient

Aluminum Zirconium Trichlorohydrex GLY 20%

Purpose

Antiperspirant

Uses

- reduces underarm wetness

Warnings

DOSAGE AND ADMINISTRATION

For external use only.

Do not use on broken skin.

Stop use if rash or irritation occurs.

Ask a doctor before use if you have kidney disease.

Keep out of reach of children.

If swallowed, get medical help or contact a Poison Control Center right away.

Directions

Apply to underarms only

Inactive ingredients

Cyclopentasiloxane, Stearyl Alcohol, PPG-14 Butyl Ether, Hydrogenated Castor Oil, Mineral Oil, Glyceryl Stearate, PEG-100 Stearate.